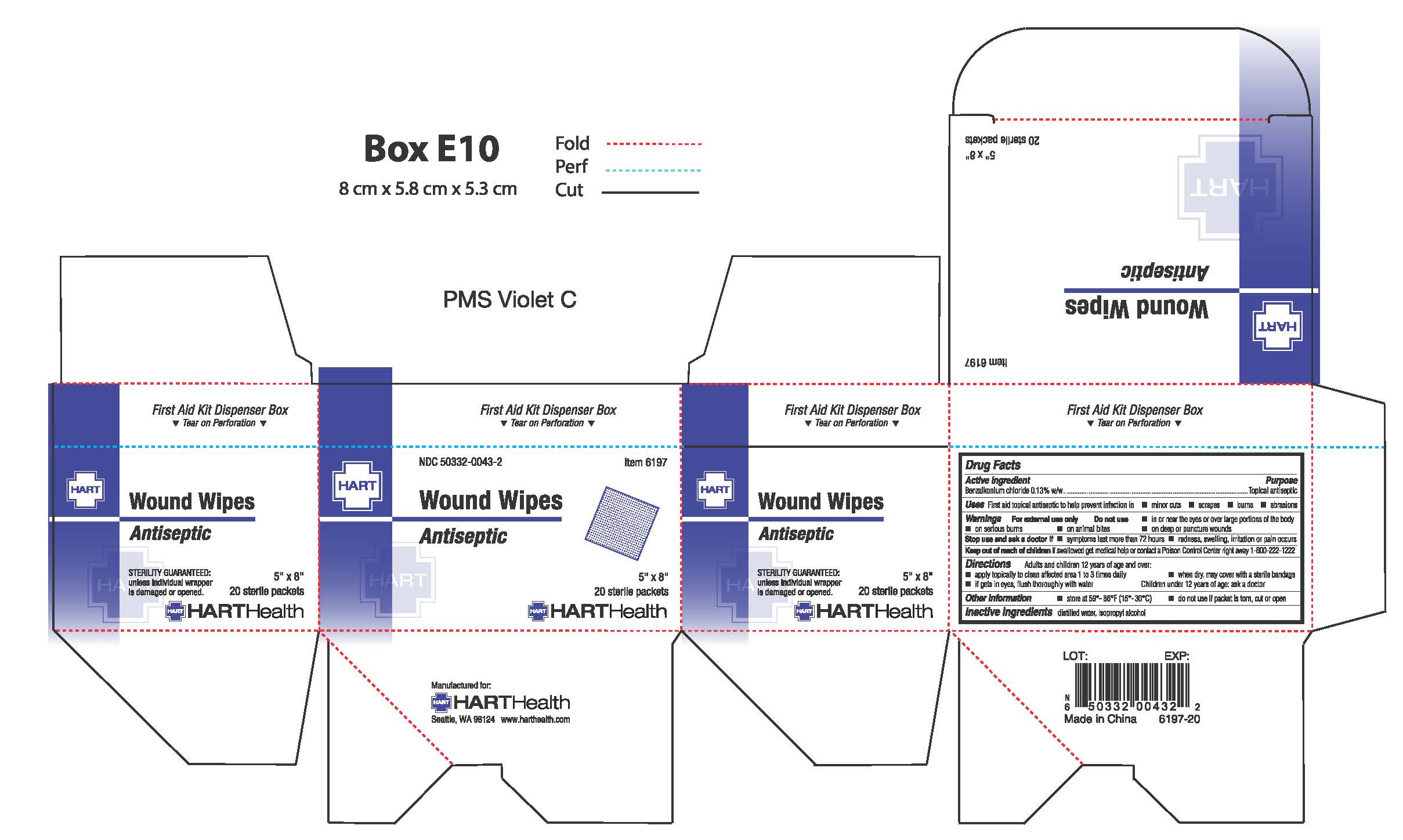 DRUG LABEL: WOUND WIPES
NDC: 50332-0043 | Form: SWAB
Manufacturer: HART Health
Category: otc | Type: HUMAN OTC DRUG LABEL
Date: 20251231

ACTIVE INGREDIENTS: BENZALKONIUM CHLORIDE .0013 g/1 g
INACTIVE INGREDIENTS: ALCOHOL; WATER

Wound Wipes

Active Ingredient

Benzalkonium Chloride 0.13% w/w

Purpose

Topical Antiseptic

Uses

First aid topical antiseptic to help prevent infection in:

- minor cuts
- scrapes
- burns
- abrasions

Warnings

For external use only

FLAMMABLE keep away from heat and flame

Do not use

- in the eyes or apply over large portions of the body
- on serious burns
- on animal bites
- on deep or puncture wounds

Stop use and ask a doctor if

- symptoms last more than 72 hours
- redness, swelling, irritation, or pain occurs

Keep out of reach of children.

If swallowed get medical help or contact a Poison Control Center right away. 1-800-222-1222

Directions

Adults and chldren 12 years of age and over:

- apply topically to the clean affected area 1 to 3 times daily
- when dry, may be covered with a sterile bandage
- if gets in eyes, flush thoroughly with water

Children under 12 years of age:

- ask a doctor

Inactive Ingredients

Alcohol, Purified Water